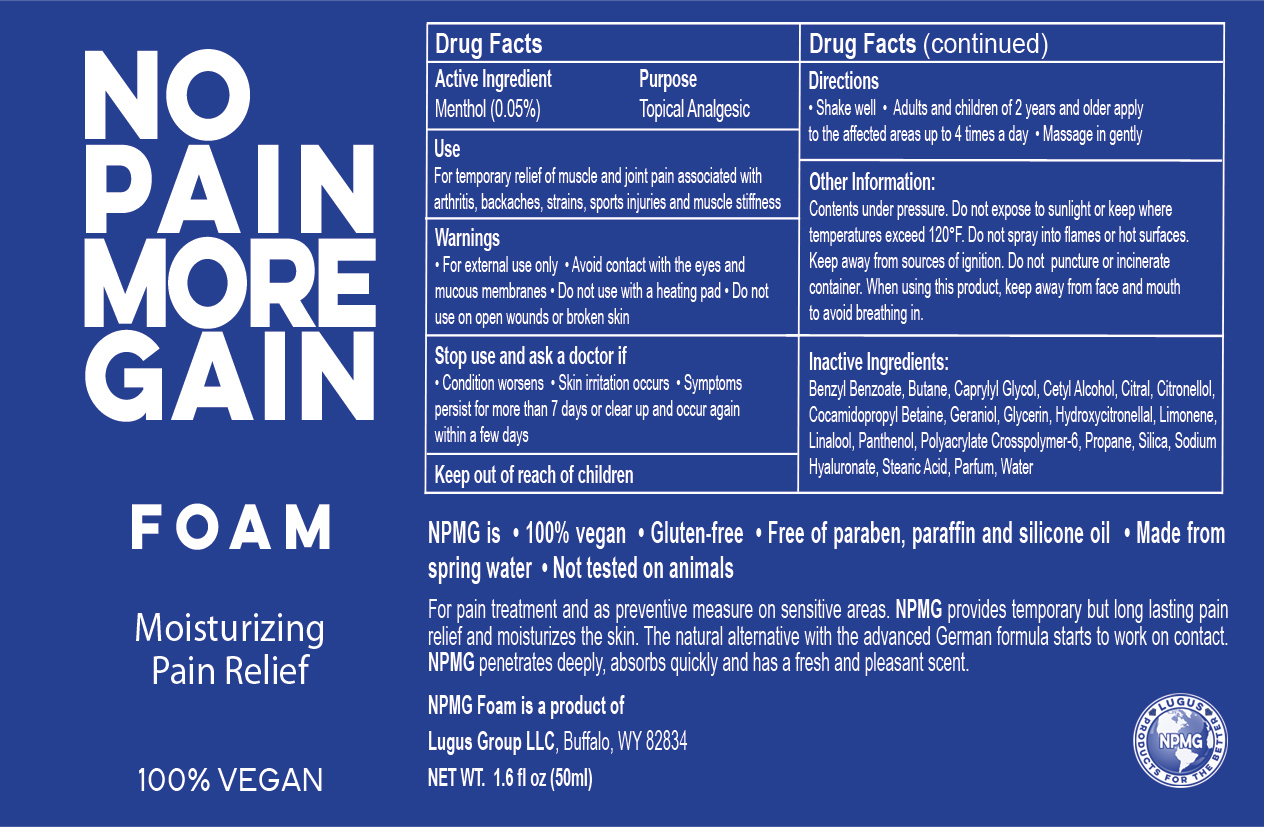 DRUG LABEL: No Pain More Gain
NDC: 69161-002 | Form: AEROSOL, FOAM
Manufacturer: Lugus Group LLC
Category: otc | Type: HUMAN OTC DRUG LABEL
Date: 20191217

ACTIVE INGREDIENTS: MENTHOL 5 mg/100 mg
INACTIVE INGREDIENTS: BUTANE; WATER; GLYCERIN; PROPANE; CETYL ALCOHOL; PANTHENOL; HYALURONATE SODIUM; STEARIC ACID; CAPRYLYL GLYCOL; SILICON DIOXIDE; COCAMIDOPROPYL BETAINE; BENZYL BENZOATE; CITRAL; .BETA.-CITRONELLOL, (R)-; GERANIOL; HYDROXYCITRONELLAL; LIMONENE, (+)-; LINALOOL, (+)-

Active Ingredient Purpose

Menthol (0.05%) Topical Analgesic

Use

For temporary relief of muscle and joint pain associated with arthritis, backaches, strains, sports injuries, muscle stiffness

Keep out of reach of children.

Directions

Shake Well. Adults and children of 2 years and older apply to the affected areas up to 4 times a day. Massage in gently.

Warnings

• For external use only • Avoid contact with the eyes and mucous membranes • Do not use with a heating pad • Do not use on open wounds or broken skin.

Inactive Ingredients

Benzyl Benzoate, Butane, Caprylyl Glycol, Cetyl Alcohol, Citral, Citronellol, Cocamidopropyl Betaine, Geraniol, Glycerin, Hydroxycitronellal, Limonene, Linalool, Panthenol, Parfum, Polyacrylate Crosspolymer-6, Propane, Silica, Sodium Hyaluronate, Stearic Acid, Water.

Other Information

Contents under pressure. Do not expose to sunlight or keep where temperatures exceed 120°F. Do not spray into flames or hot surfaces. Keep away from sources of ignition. Do not puncture or incinerate container. When using this product, keep away from face and mouth to avoid breathing in.

INDICATIONS AND USAGE

100% Vegan

No Pain More Gain Foam

Moisturizing Pain Relief

NPMG is • 100% vegan • Gluten-free • Free of paraben, paraffin and silicone oil • Made from spring water • Not tested on animals

For pain treatment and as preventive measure on sensitive areas. NPMG provides temporary but long lasting pain relief and moisturizes the skin. The natural alternative with the advanced German formula starts to work on contact. NPMG penetrates deeply, absorbs quickly and has a fresh and pleasant scent.

NPMG Foam is a product of

Lugus Group LLC, Buffalo, WY 82834

NET WT 2.5 fl oz (75 ml)

Stop use and ask a doctor if

• Condition worsens • skin irritation occurs • Symptoms persist for more than 7 days or clear up and occur again within a few days